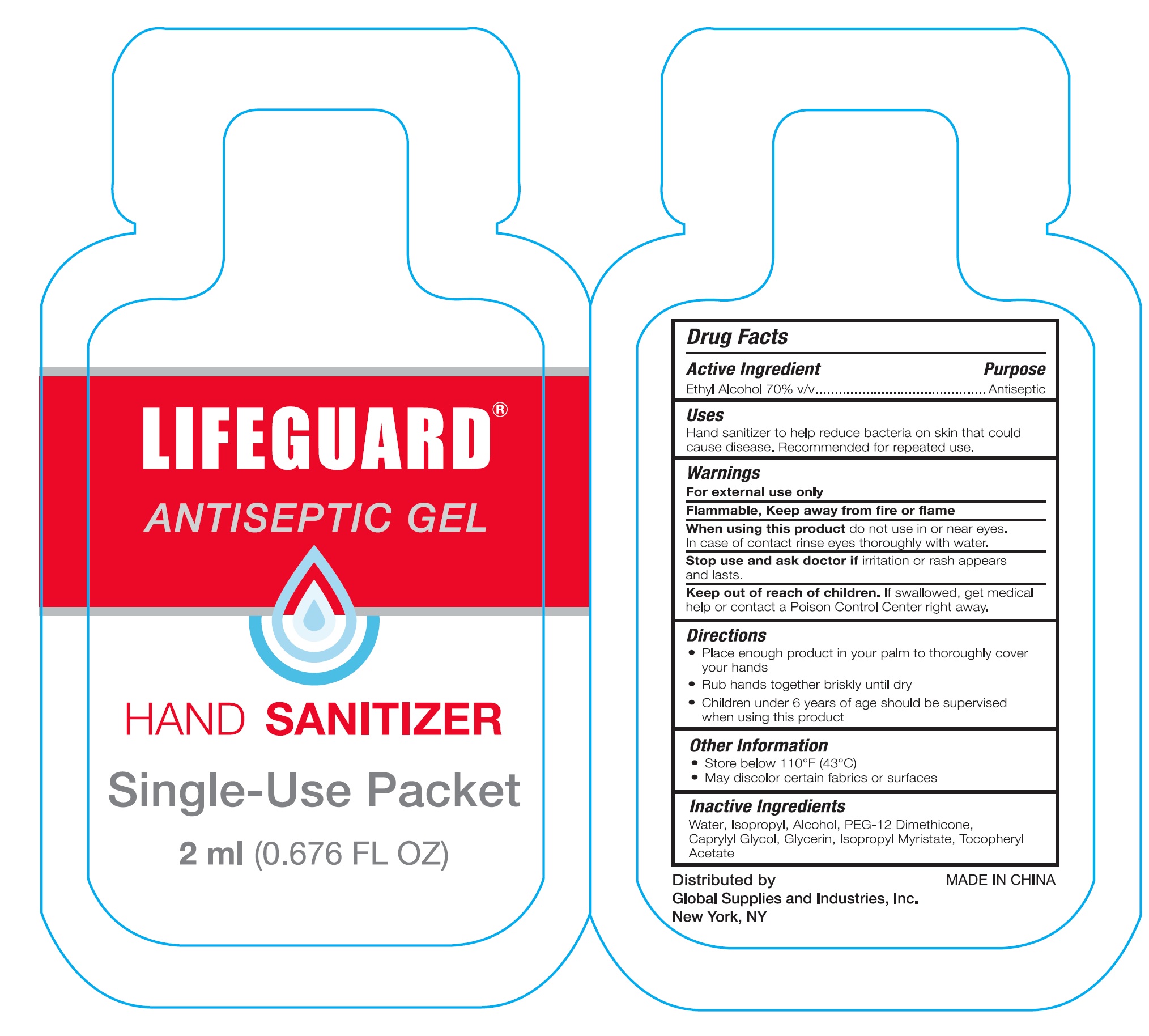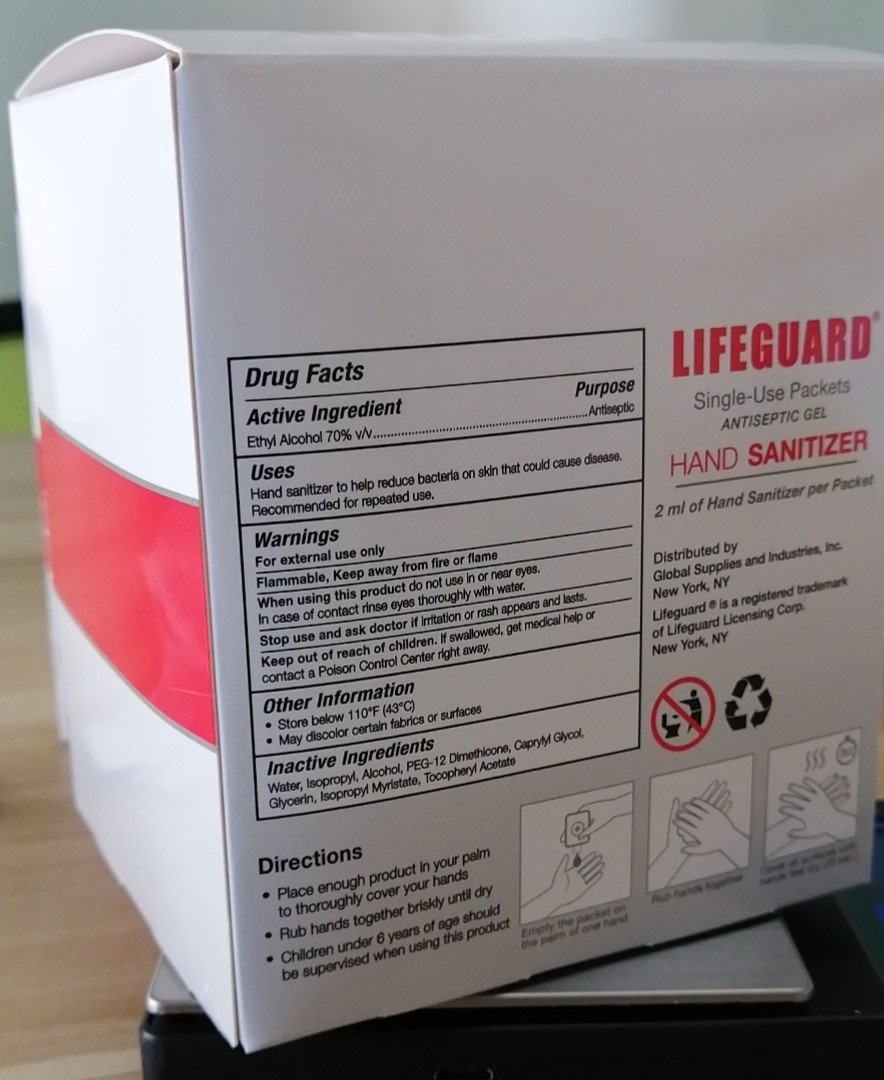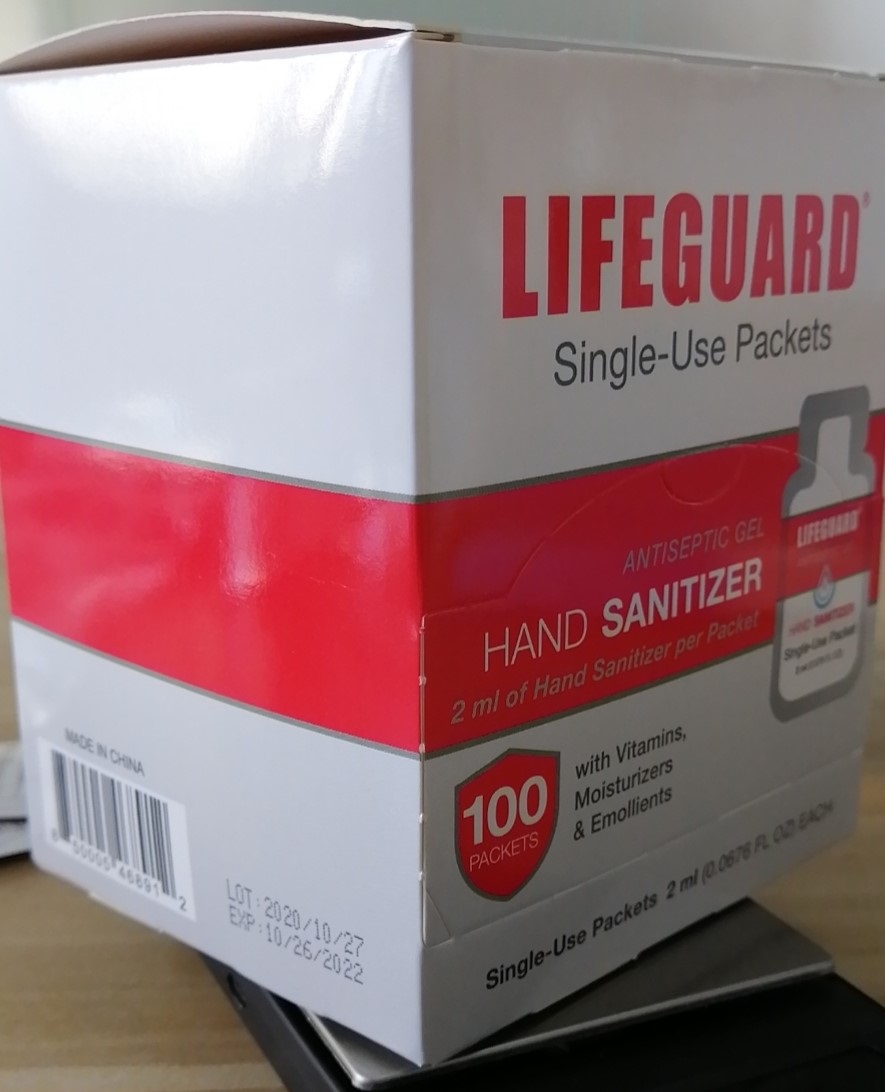 DRUG LABEL: LFG-IND-SAN Single Use Sanitizer Packet
NDC: 77879-004 | Form: GEL
Manufacturer: BT Supplies West Inc
Category: otc | Type: HUMAN OTC DRUG LABEL
Date: 20220209

ACTIVE INGREDIENTS: ALCOHOL 0.7 mL/1 mL
INACTIVE INGREDIENTS: WATER; ISOPROPYL ALCOHOL; PEG-12 DIMETHICONE; CAPRYLYL GLYCOL; GLYCERIN; ISOPROPYL MYRISTATE; .ALPHA.-TOCOPHEROL ACETATE

LFG-IND-SAN Single Use Sanitizer Packet

Active Ingredient

Ethyl Alcohol 70% v/v

Purpose

Antiseptic

Uses

Hand sanitizer to help reduce bacteria on skin that could cause disease. Recommended for repeated use.

Warnings

For external use only
Flammabl, Keep away from fire or flame

When using this product

do not use in or near eyes. In case of contact rinse eyes thoroughly with water.

Stop use and ask a doctor if

irritation or rash appears and lasts.

Keep out of reach of children.

If swallowed, get medical help or contact a Poison Control Center right away.

Directions

- Place enough product in your palm to thoroughly cover your hands
- Rub hands together briskly until dry
- Children under 6 years of age should be supervised when using this product

Other Information

- Store below 110°F (43°C)
- May discolor certain fabrics or surfaces

Inactive Ingredients

Water, Isopropyl Alcohol, PEG-12 Dimethicone, Caprylyl Glycol, Glycerin, Isopropyl Myristate, Tocopheryl Acetate